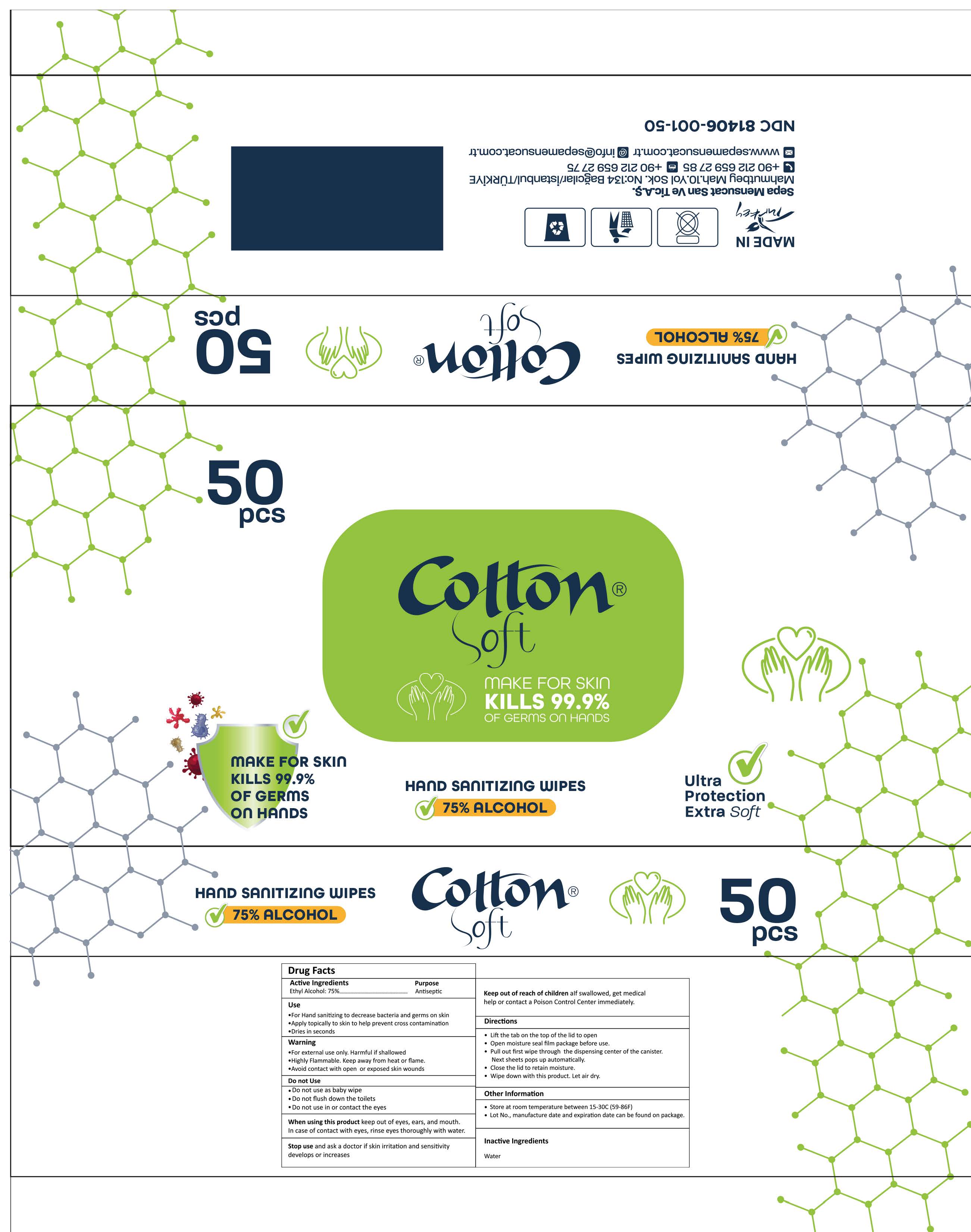 DRUG LABEL: Cotton Soft
NDC: 81406-001 | Form: CLOTH
Manufacturer: SEPA MENSUCAT SANAYI VE TICARET ANONIM SIRKETI
Category: otc | Type: HUMAN OTC DRUG LABEL
Date: 20211025

ACTIVE INGREDIENTS: ALCOHOL 75 g/100 g
INACTIVE INGREDIENTS: WATER 25 g/100 g

HAND SANITIZING WIPES

This is a hand sanitizer manufactured according to the Temporary Policy for Preparation of Certain Alcohol-Based Hand Sanitizer Products During the Public Health Emergency (CoViD-19); Guidance for Industry.

The hand sanitizer is manufactured using only the following United States Pharmacopoeia (USP) grade ingredients in the preparation of the product (percentage in final product formulation) consistent with World Health Organization (WHO) recommendations:

1. Alcohol (ethanol) (USP or Food Chemical Codex (FCC) grade) (80%, volume/volume (v/v)) in an aqueous solution denatured according to Alcohol and Tobacco Tax and Trade Bureau regulations in 27 CFR part 20.
2. Glycerol (1.45% v/v).
3. Hydrogen peroxide (0.125% v/v).
4. Sterile distilled water or boiled cold water.

The firm does not add other active or inactive ingredients. Different or additional ingredients may impact the quality and potency of the product.

Active Ingredient(s)

Ethyl Alcohol 75%. Purpose: Antiseptic

Purpose

Antiseptic, Hand Sanitizer

Use

For Hand sanitizing to decrease bacteria and germs on skin

Apply topically to skin to help prevent cross contamination

Dries in seconds

Warnings

For external use only. Harmful if shallowed

Highly Flammable.

Keep away from heat or flame.

Avoid contact with open or exposed skin wounds

- Do not use as baby wipes
- Do not flush down the toilets
- Do not use in or contact the eyes

When using this product keep out of eyes, ears, and mouth. In case of contact with eyes, rinse eyes thoroughly with water.
Stop use and ask a doctor if skin irritation and sensitivity develops or increases.
Keep out of reach of children. If swallowed, get medical help or contact a Poison Control Center immediately.

Stop use and ask a doctor if skin irritation and sensitivity develops or increases.

Keep out of reach of children. If swallowed, get medical help or contact a Poison Control Center immediately.

Directions

- Lift the tab on the top of the lid to open
- Open moisture seal film package before use.
- Pull out first wipe through the dispensing center of the canister. Next sheets pops up automatically.
- Close the lid to retain moisture.
- Wipe down with this product. Let air dry.

Other information

- Store at room temperature between 15-30C (59-86F)
- Lot No., manufacture date and expiration date can be found on package.

Inactive ingredients

Purified water

Hand Sanitizing wipes-Package Label - Principal Display Panel

Hand Sanitizing wipes 50 pcs NDC: 81406-001

Hand Sanitizing Wipes- 50 pcs

NDC: 81406-001-50